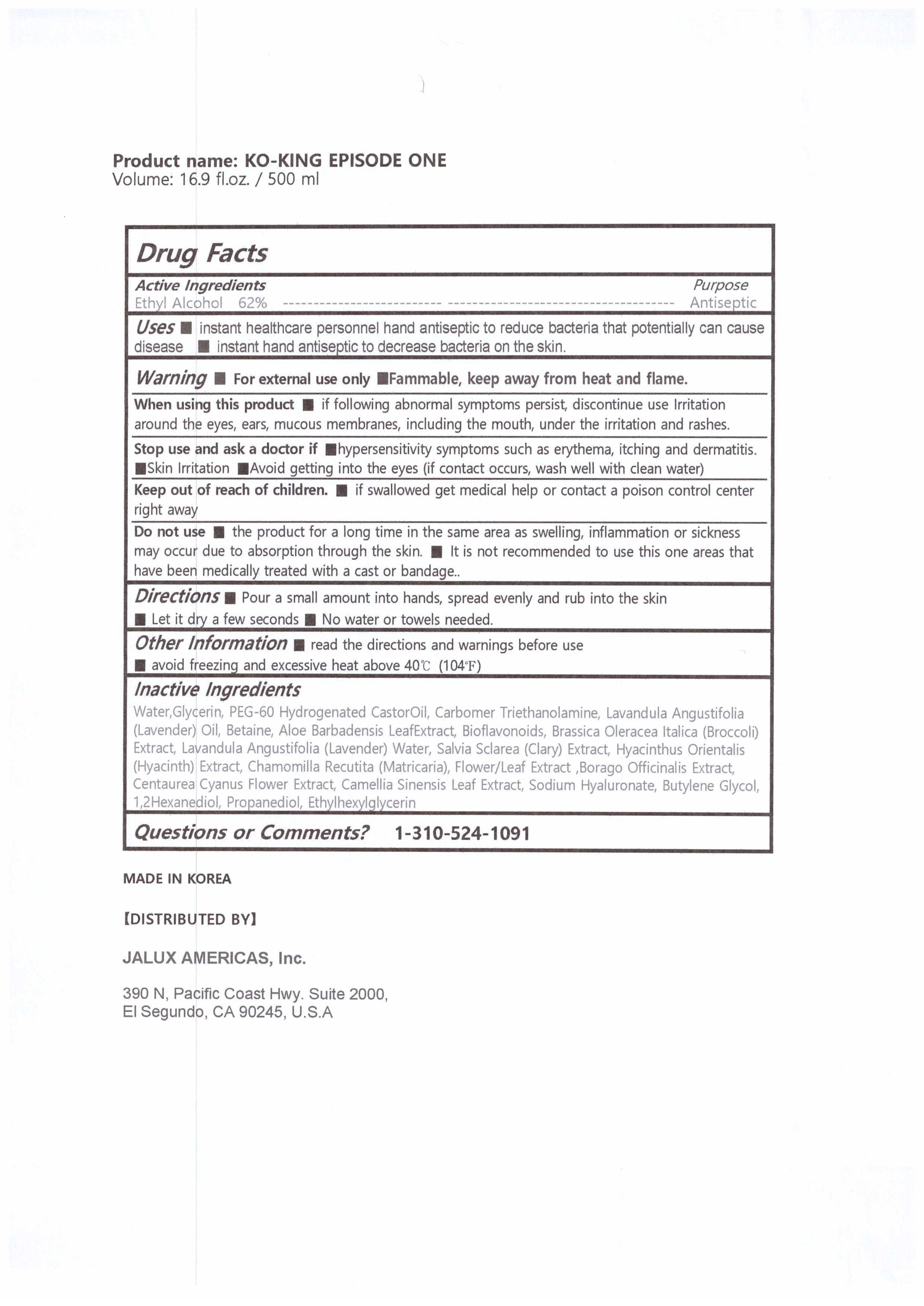 DRUG LABEL: KO-KING EPISODE ONE
NDC: 78488-0005 | Form: GEL
Manufacturer: JNJ COSTEC CO
Category: otc | Type: HUMAN OTC DRUG LABEL
Date: 20201124

ACTIVE INGREDIENTS: ALCOHOL 62 mL/100 mL
INACTIVE INGREDIENTS: PEG-60 HYDROGENATED CASTOR OIL; WATER; CARBOMER 940; TROLAMINE; BUTYLENE GLYCOL; 1,2-HEXANEDIOL; GLYCERIN; ETHYLHEXYLGLYCERIN

Drug Facts

ACTIVE INGREDIENT

Alcohol

INACTIVE INGREDIENT

Water
Glycerin
PEG-60 Hydrogenated Castor Oil
Carbomer
Triethanolamine
Sodium Hyaluronate
Tocopherol
Butylene Glycol
1,2-Hexanediol

ETC

PURPOSE

Instantly kils most common germs and bacteria without damaging skin and stop some viruses.
Great alternative when soap and water are not available.
Disposable and quick-drying.
Perfect and convenient to carry in purse, school backpacks and travel bags.

KEEP OUT OF REACH OF THE CHILDREN

INDICATIONS AND USAGE

Just apply it, let it dry a few seconds. No water or towels needed.

WARNINGS

1. Do not use this product on the following parts of body. Around eyes and ears, oral cavity, large area of the
parts of body, or wounded skins (It may cause irritations)
2. Stop using at once in case of the following symptoms, and seek medical advice. 1) When eczema, red spots,
itchiness, edema, and allergic reactions occur. 2)When skin irritations happen.
3. Other user reminders 1) For external use only(No oral intake). 2) Avoid contact with eyes, and in case contact
occurs, rinse it thoroughly with clean water and consult a doctor or pharmacist. 3) When you use it on a large skin
area or use it long-termly, please be aware that vapor is not absorbed. (If Ethanol vapor is largely and repeatedly
inhaled and absorbed, it may cause irritation to mucous membrane and headache might occur.) 4)When the product
is used on the same part of skin repeatedly, the skin may become rough due to skimming. 5) Do not use with sealed
gauze bandage, Gibbs bandage or pack, as irritations may occur. 6) Do not use this product while anus and vagina
steaming as irritations or chemical burns may occur. 7) Do not use for purposes other than specified.

DOSAGE AND ADMINISTRATION

external use only